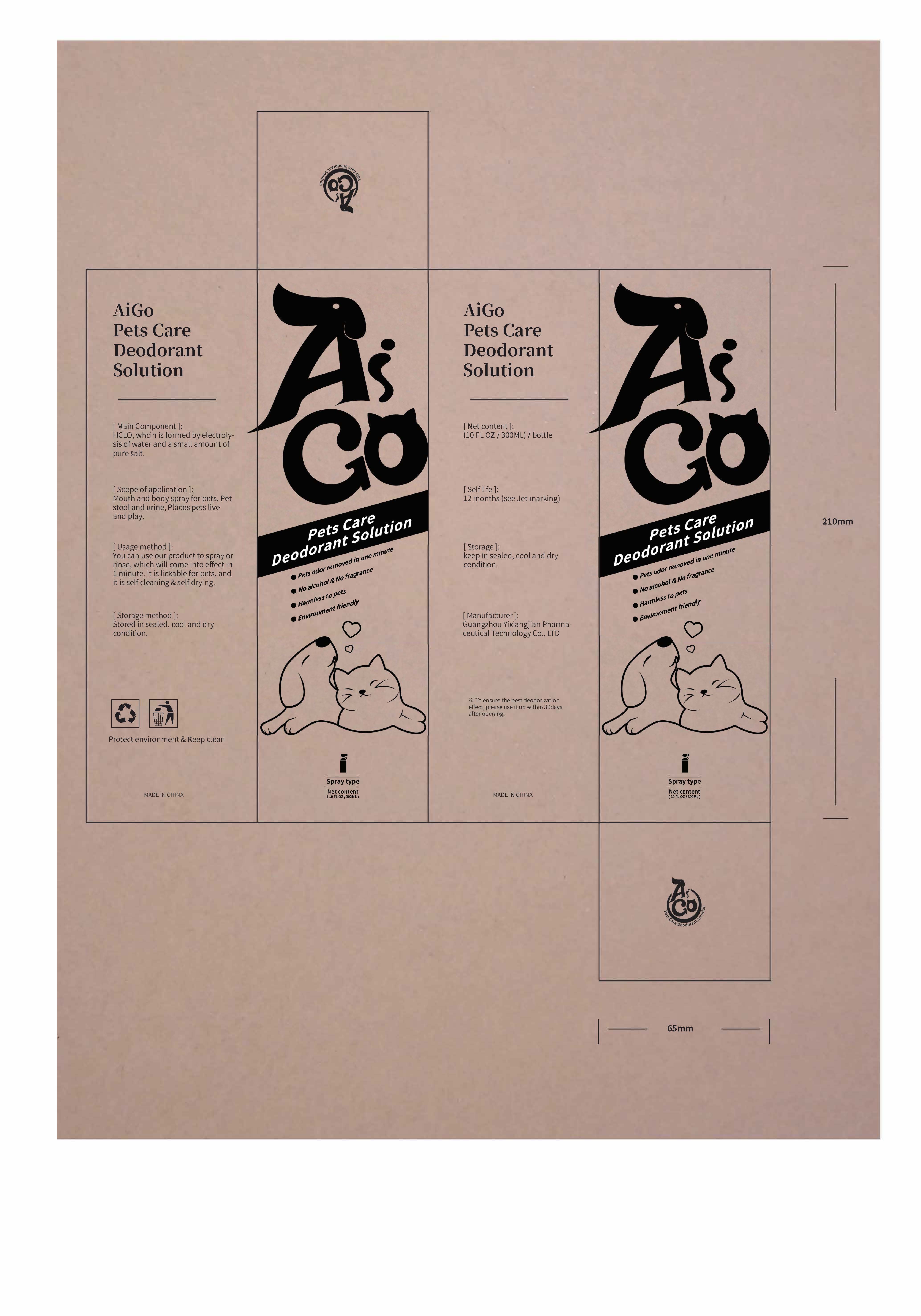 DRUG LABEL: Pet deodorant care solution
NDC: 41935-002 | Form: liquid
Manufacturer: Guangzhou Yixiangjian Information Technology Co., Ltd.
Category: animal | Type: OTC ANIMAL DRUG LABEL
Date: 20230215

ACTIVE INGREDIENTS: HYPOCHLOROUS ACID 1 g/10 mL
INACTIVE INGREDIENTS: water 9 g/10 mL

Active ingredients

HYPOCHLOROUS ACID

Inactive ingredients

WATER

PURPOSE

Pets and pet environment deodorization

KEEP OUT OF REACH OF CHILDREN

When not in use, place the product in a place that children cannot reach

INDICATIONS AND USAGE

Odor from pets and pet environment

WARNINGS

Do not eat it. If you eat it by mistake, please consult a doctor as soon as possible

DOSAGE AND ADMINISTRATION

When the pet has a bad smell with the pet environment, spray it several times a day, depending on the environment

OTHER SAFETY INFORMATION

Store it in a cool place, and use it one month after opening the bottle